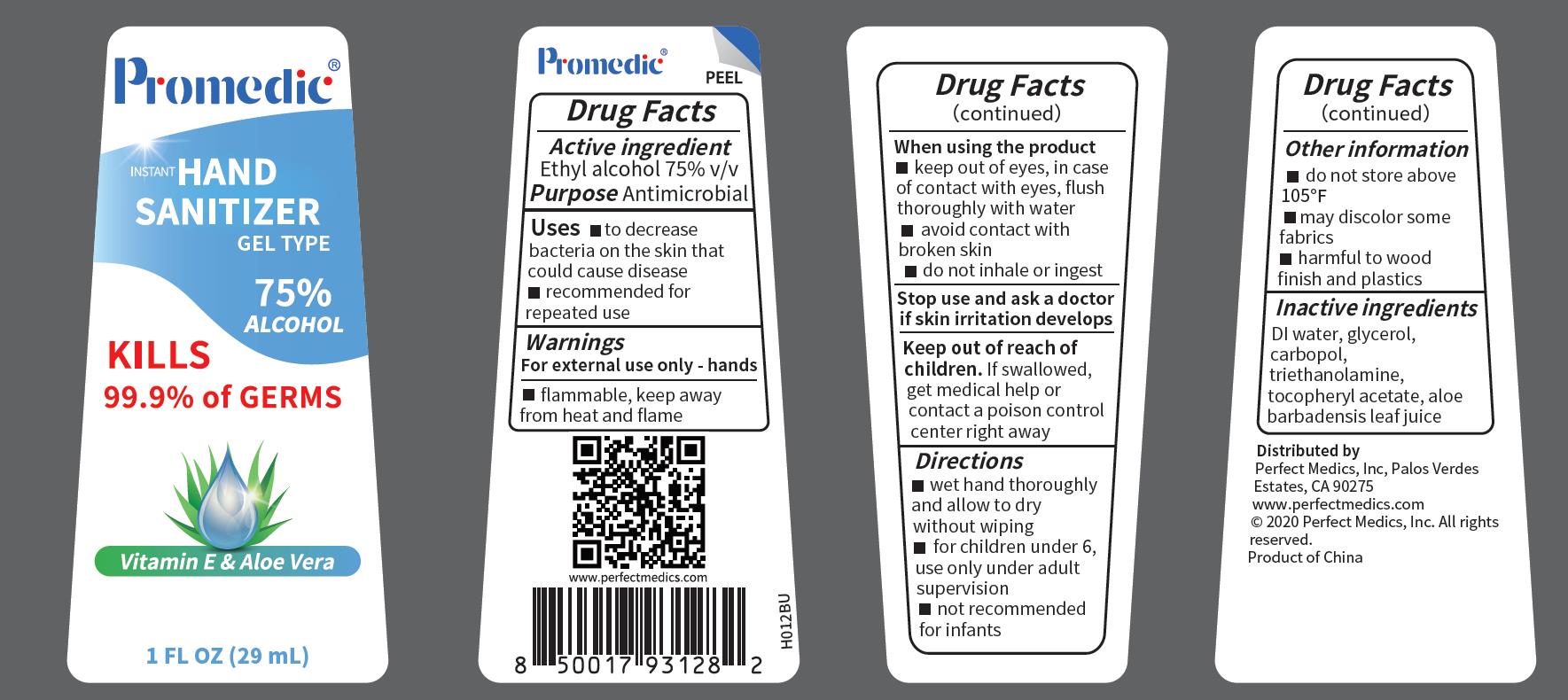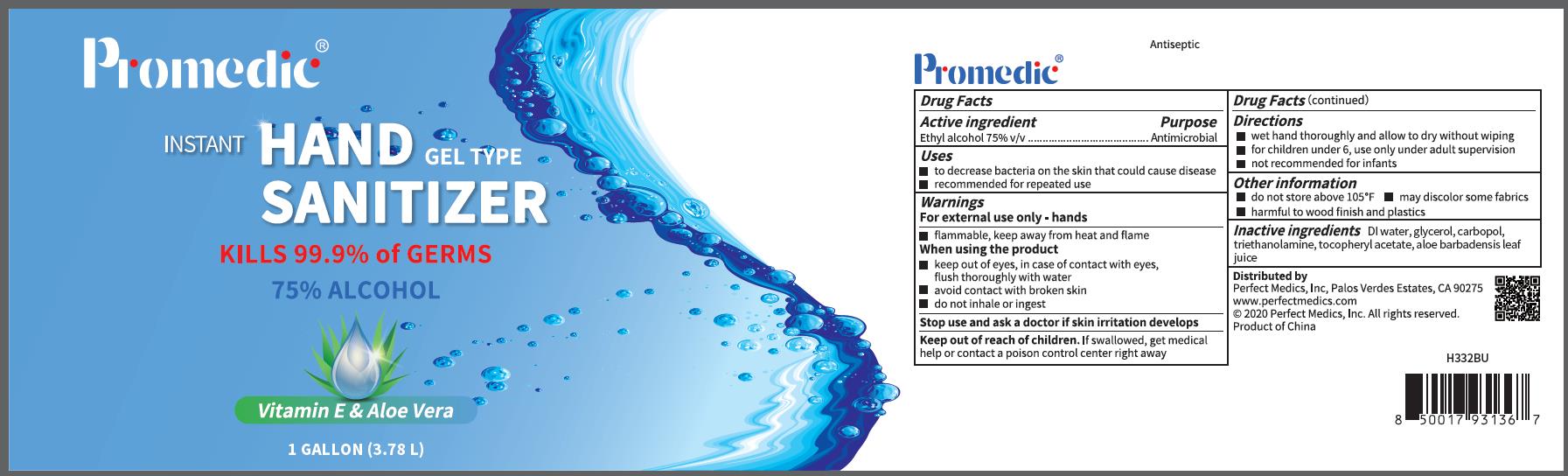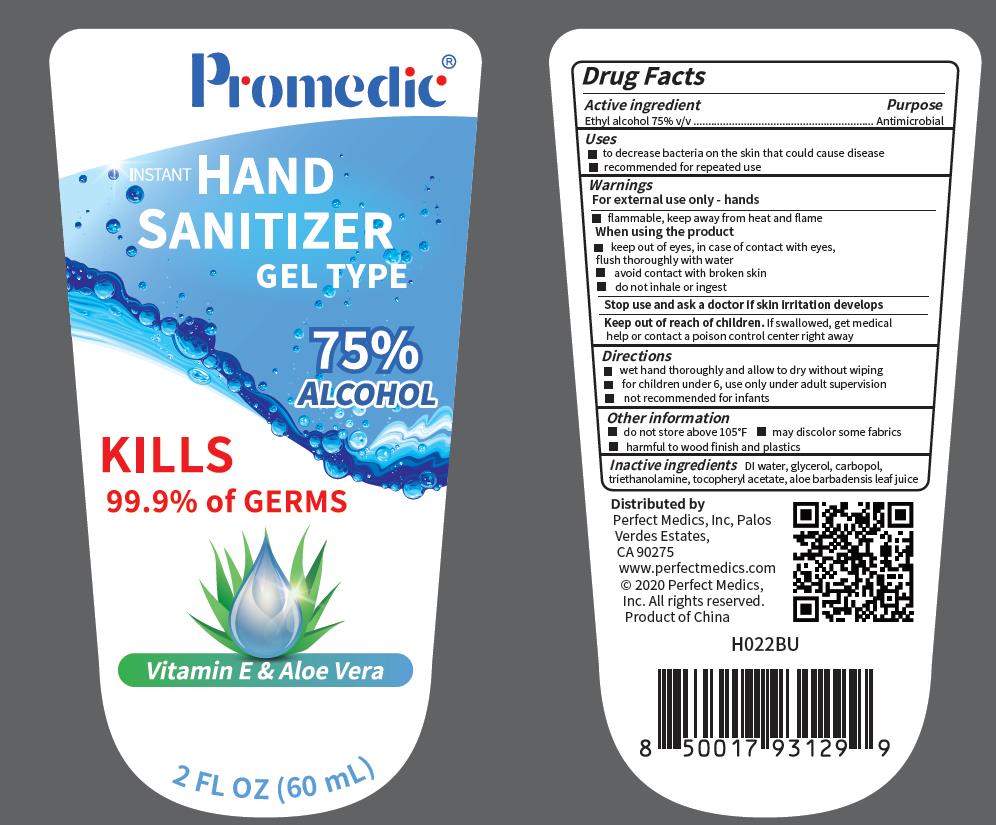 DRUG LABEL: INSTANT HAND SANITIZER
NDC: 79134-005 | Form: GEL
Manufacturer: PERFECT MEDICS, INC
Category: otc | Type: HUMAN OTC DRUG LABEL
Date: 20200915

ACTIVE INGREDIENTS: ALCOHOL 21.75 mL/29 mL
INACTIVE INGREDIENTS: WATER 6.73 mL/29 mL; GLYCERIN 0.29 mL/29 mL; POLYACRYLIC ACID (250000 MW) 0.1015 mL/29 mL; TROLAMINE 0.0725 mL/29 mL; .ALPHA.-TOCOPHEROL ACETATE 0.0029 mL/29 mL; ALOE VERA LEAF 0.058 mL/29 mL

Active Ingredient(s)

Alcohol 75% v/v. Purpose: Antimicrobial

Purpose

Antiseptic

Use

to decrease bacteria on the skin that could cause disease;recommended for repeated use

Warnings

For external use only-hands. Flammable. Keep away from heat or flame

Do not use

- in children less than 2 months of age
- on open skin wounds

When using this product keep out of eyes. In case of contact with eyes flush thoroughly with water;avoid contact with broken skin;do not inhale or ingest
Stop use and ask a doctor if skin irritation develops.
Keep out of reach of children. If swallowed, get medical help or contact a Poison Control Center right away.

Stop use and ask a doctor if skin irritation develops.

Keep out of reach of children. If swallowed, get medical help or contact a Poison Control Center right away.

Directions

- wet hand thoroughly and allow to dry without wiping
- for children under6, use only under adult supervision
- not recommended for infants

Other information

do not store above 105℉;

may discolor some fabrics

harmful to wood finish and plastic

Inactive ingredients

DI water,glycerin, carbopol,triethanolamine,tocopheryl acetate,aloe barbadensis leaf juice

Package Label - Principal Display Panel

Package Label